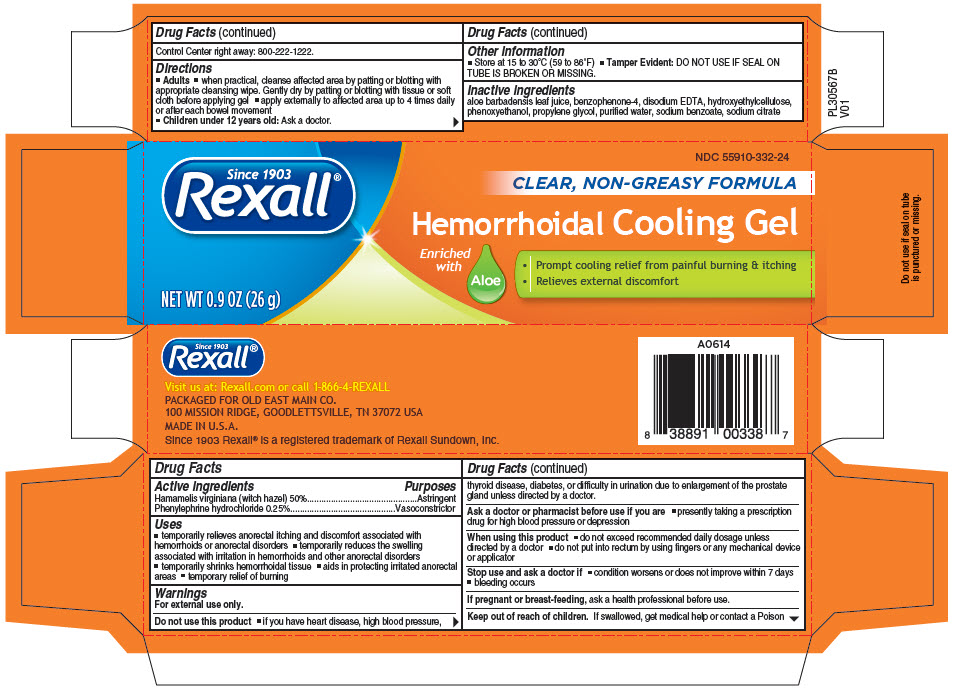 DRUG LABEL: Rexall Hemorrhoidal Cooling Gel
NDC: 55910-332 | Form: CREAM
Manufacturer: DOLGENCORP, LLC
Category: otc | Type: HUMAN OTC DRUG LABEL
Date: 20241217

ACTIVE INGREDIENTS: Witch Hazel 0.5 mg/1 g; Phenylephrine Hydrochloride 0.0025 mg/1 g
INACTIVE INGREDIENTS: Aloe Vera Leaf; Benzophenone; Edetate Disodium; Hydroxyethyl Cellulose (280 Mpa.S At 2%); Propylene Glycol; Water; Anhydrous Trisodium Citrate

Rexall® Hemorrhoidal Cooling Gel
Topical

Drug Facts

ACTIVE INGREDIENT

PURPOSE

Active ingredients | Purposes
Hamamelis virginiana (witch hazel) 50% | Astringent
Phenylephrine hydrochloride 0.25% | Vasoconstrictor

Uses

- temporarily relieves anorectal itching and discomfort associated with hemorrhoids or anorectal disorders
- temporarily reduces the swelling associated with irritation in hemorrhoids and other anorectal disorders
- temporarily shrinks hemorrhoidal tissue
- aids in protecting irritated anorectal areas
- temporary relief of burning

Warnings

For external use only.

Do not use this product

- if you have heart disease, high blood pressure, thyroid disease, diabetes, or difficulty in urination due to enlargement of the prostate gland unless directed by a doctor.

Ask a doctor or pharmacist before use if you are

- presently taking a prescription drug for high blood pressure or depression

When using this product

- do not exceed recommended daily dosage unless directed by a doctor
- do not put into rectum by using fingers or any mechanical device or applicator

Stop use and ask a doctor if

- condition worsens or does not improve within 7 days
- bleeding occurs

PREGNANCY OR BREAST FEEDING

If pregnant or breast-feeding, ask a health professional before use.

Keep out of reach of children. If swallowed, get medical help or contact a Poison Control Center right away: 800-222-1222.

Directions

- Adults
  - when practical, cleanse affected area by patting or blotting with appropriate cleansing wipe. Gently dry by patting or blotting with tissue or soft cloth before applying gel
  - apply externally to affected area up to 4 times daily or after each bowel movement
- Children under 12 years old: Ask a doctor.

Other information

- Store at 15 to 30°C (59 to 86°F)
- Tamper Evident: DO NOT USE IF SEAL ON TUBE IS BROKEN OR MISSING.

Inactive ingredients

aloe barbadensis leaf juice, benzophenone-4, disodium EDTA, hydroxyethylcellulose, phenoxy ethenol, propylene glycol, purified water, sodium benzoate, sodium citrate

PRINCIPAL DISPLAY PANEL - 26 g Tube Carton

NDC 55910-332-24

Since 1903
Rexall®

CLEAR, NON-GREASY FORMULA

Hemorrhoidal Cooling Gel

Enriched
with
Aloe

- Prompt cooling relief from painful burning & itching
- Relieves external discomfort

NET WT 0.9 OZ (26 g)